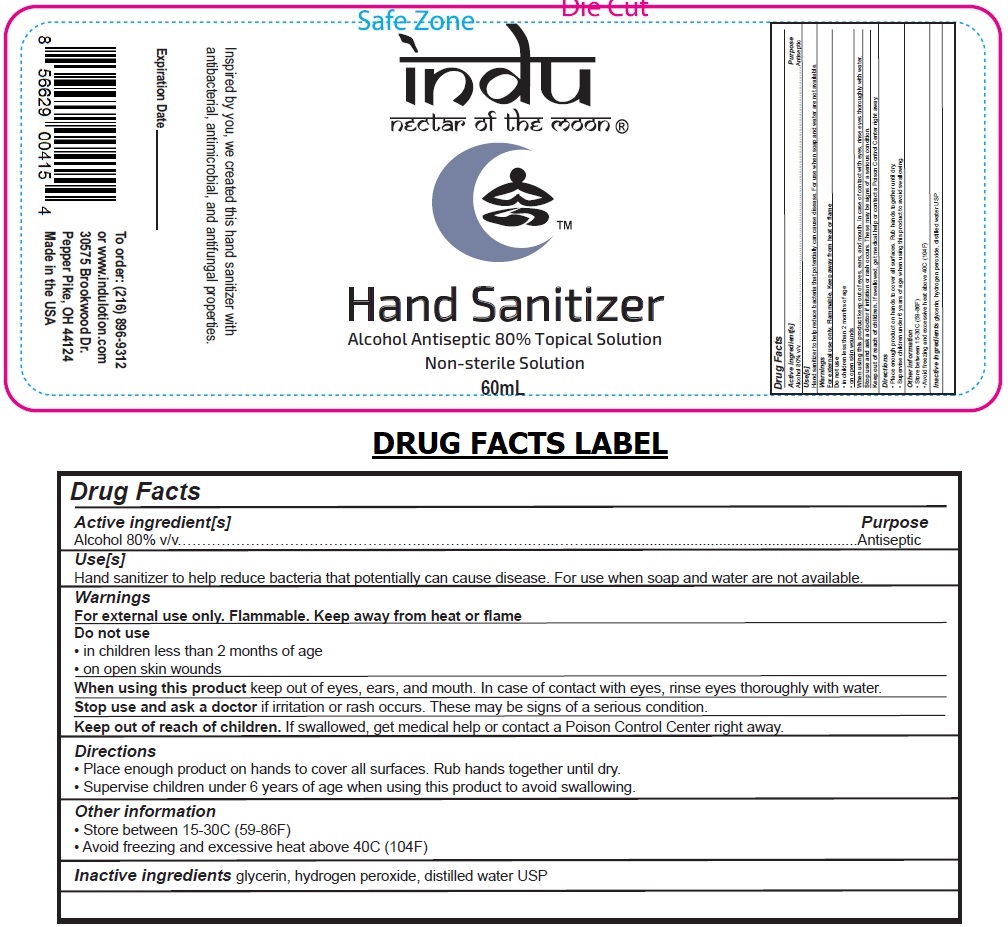 DRUG LABEL: Indu Hand Sanitizer
NDC: 90040-101 | Form: SPRAY
Manufacturer: Indu Aromatherapy LLC
Category: otc | Type: HUMAN OTC DRUG LABEL
Date: 20200825

ACTIVE INGREDIENTS: ALCOHOL 80 mL/100 mL
INACTIVE INGREDIENTS: GLYCERIN; HYDROGEN PEROXIDE; WATER

Indu Hand Sanitizer

Active ingredient[s]

Alcohol 80% v/v

Purpose

Antiseptic

Use[s]

Hand sanitizer to help reduce bacteria that potentially can cause disease. For use when soap and water are not available.

Warnings

For external use only. Flammable. Keep away from heat or flame

Do not use

• in children less than 2 months of age

• on open skin wounds

When using this product keep out of eyes, ears, and mouth. In case of contact with eyes, rinse eyes thoroughly with water.

Stop use and ask a doctor if irritation or rash occurs. These may be signs of a serious condition.

Keep out of reach of children. If swallowed, get medical help or contact a Poison Control Center right away.

Directions

• Place enough product on hands to cover all surfaces. Rub hands together until dry.

• Supervise children under 6 years of age when using this product to avoid swallowing.

Other information

• Store between 15-30C (59-86F)

• Avoid freezing and excessive heat above 40C (104F)

Inactive ingredients glycerin, hydrogen peroxide, distilled water USP

Alcohol Antiseptic 80% Topical Solution

Non-sterile Solution

Inspired by you, we created this hand sanitizer with antibacterial, antimicrobial, and antifungal properties.

To order: (216) 896-9312

or www.indulotion.com

30575 Brookwood Dr.

Pepper Pike, OH 44124

Made in the USA